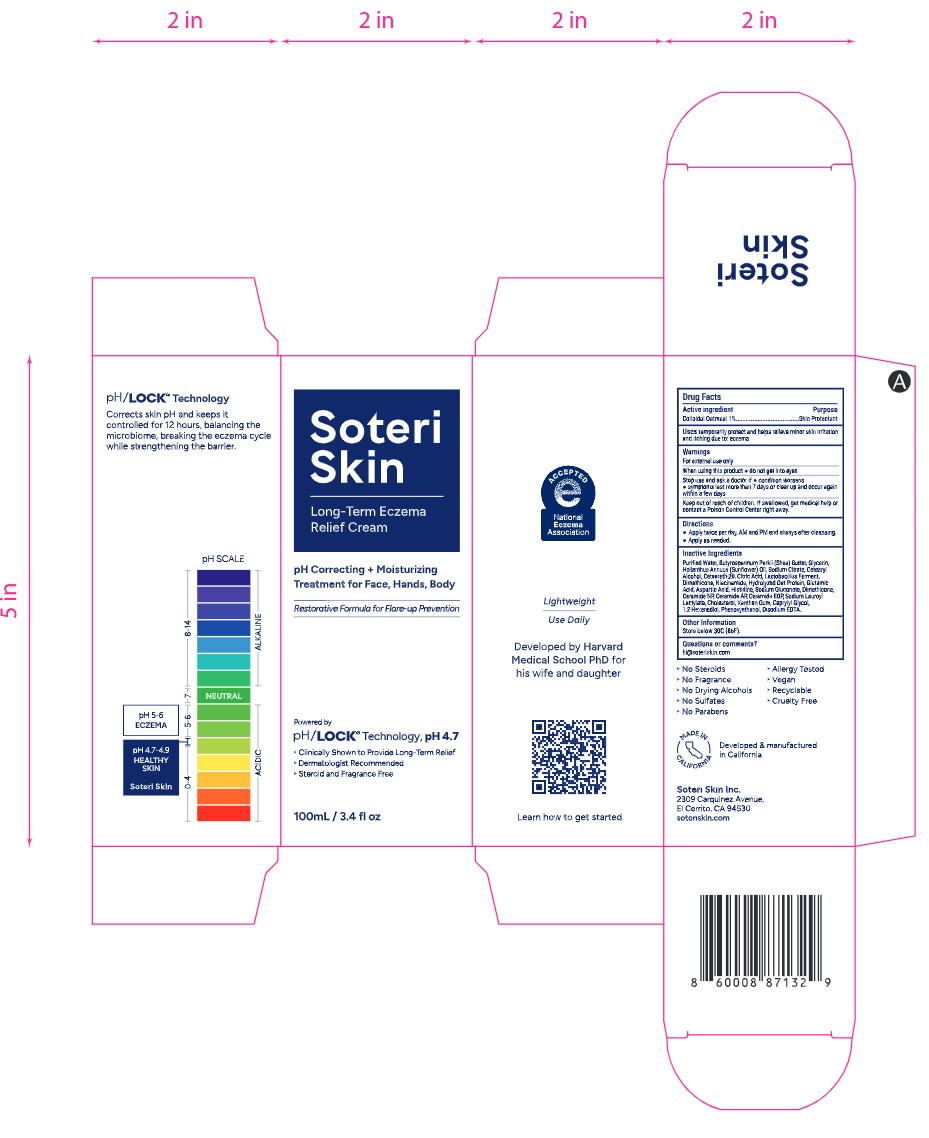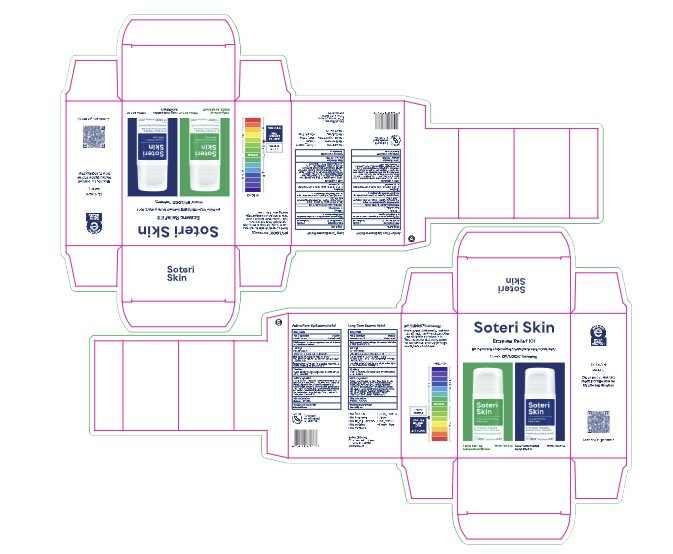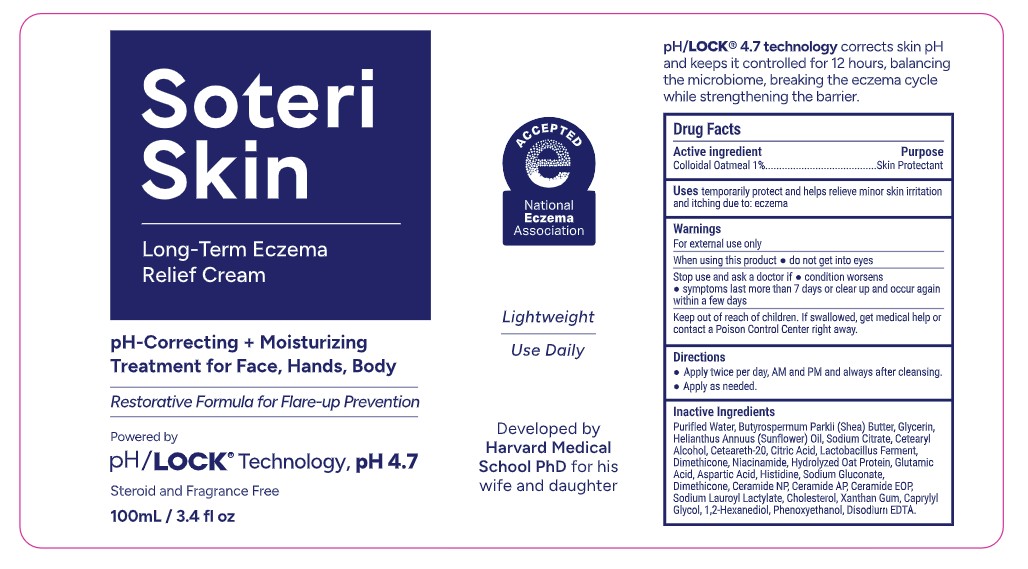 DRUG LABEL: Soteri Skin Long-Term Eczema Relief Cream
NDC: 85265-103 | Form: EMULSION
Manufacturer: Soteri Skin, Inc
Category: otc | Type: HUMAN OTC DRUG LABEL
Date: 20251209

ACTIVE INGREDIENTS: OATMEAL 1 g/100 mL
INACTIVE INGREDIENTS: WATER; SODIUM LAUROYL LACTYLATE; CHOLESTEROL; ASPARTIC ACID; 1,2-HEXANEDIOL; ANHYDROUS CITRIC ACID; PHENOXYETHANOL; BUTYROSPERMUM PARKII (SHEA) BUTTER; SODIUM CITRATE; NIACINAMIDE; SODIUM GLUCONATE; HELIANTHUS ANNUUS (SUNFLOWER) SEED OIL; OAT; GLYCERIN; LACTOBACILLUS; DIMETHICONE; CETEARYL ALCOHOL; EDETATE DISODIUM; CERAMIDE NP; CERAMIDE 1; XANTHAN GUM; CERAMIDE AP; CETEARETH-20; CAPRYLYL GLYCOL; GLUTAMIC ACID; HISTIDINE

Soteri Skin Long-Term Eczema Relief Cream NDC 85265-103

Active Ingredient

Colloidal Oatmeal 1.5%

Purpose

Skin Protectant

Uses

temporarily protect and helps relieve minor skin irritation and itching due to: eczema

Warning

For external use only

When using this product

- do not get into eyes

Stop use and ask a doctor if:

- condition worsens
- symptoms last more than 7 days or clear up and occur again within a few days

Keep out of reach of chidren

Keep out of reach of children. If swallowed, get medical help or contact a Poison Control Center right away.

Directions

- Apply twice per day, AM and PM and always after cleansing
- Apply as needed

Inactive Ingredients

Purified Water, Butyrospermum Parkii (Shea) Butter, Glycerin, Helianthus Annuus (Sunflower) Oil, Sodium Citrate, Cetearyl Alcohol, Ceteareth-20, Citric Acid, Lactobacillus Ferment, Dimethicone, Niacinamide, Hydrolyzed Oat Protein, Glutamic Acid, Aspartic Acid, Histidine, Sodium Gluconate, Dimethicone, Ceramide NP, Ceramide AP, Ceramide EOP, Sodium Lauroyl Lactylate, Cholesterol, Xanthan Gum, Caprylyl Glycol, 1,2-Hexanediol, Phenoxyethanol, Disodium EDTA.

Other Information

Store below 30C (86F)